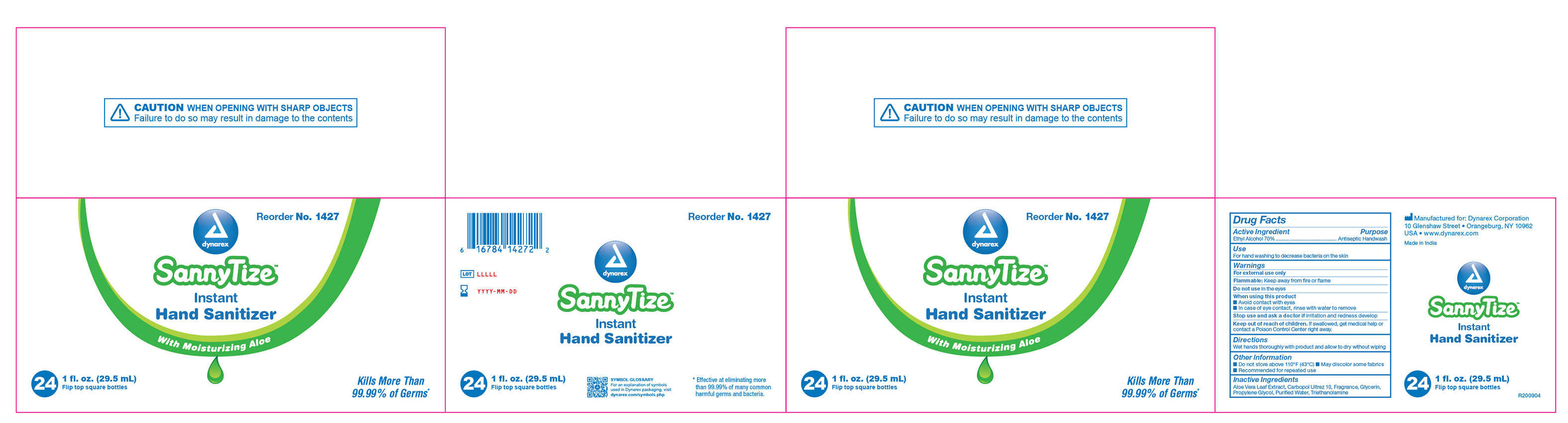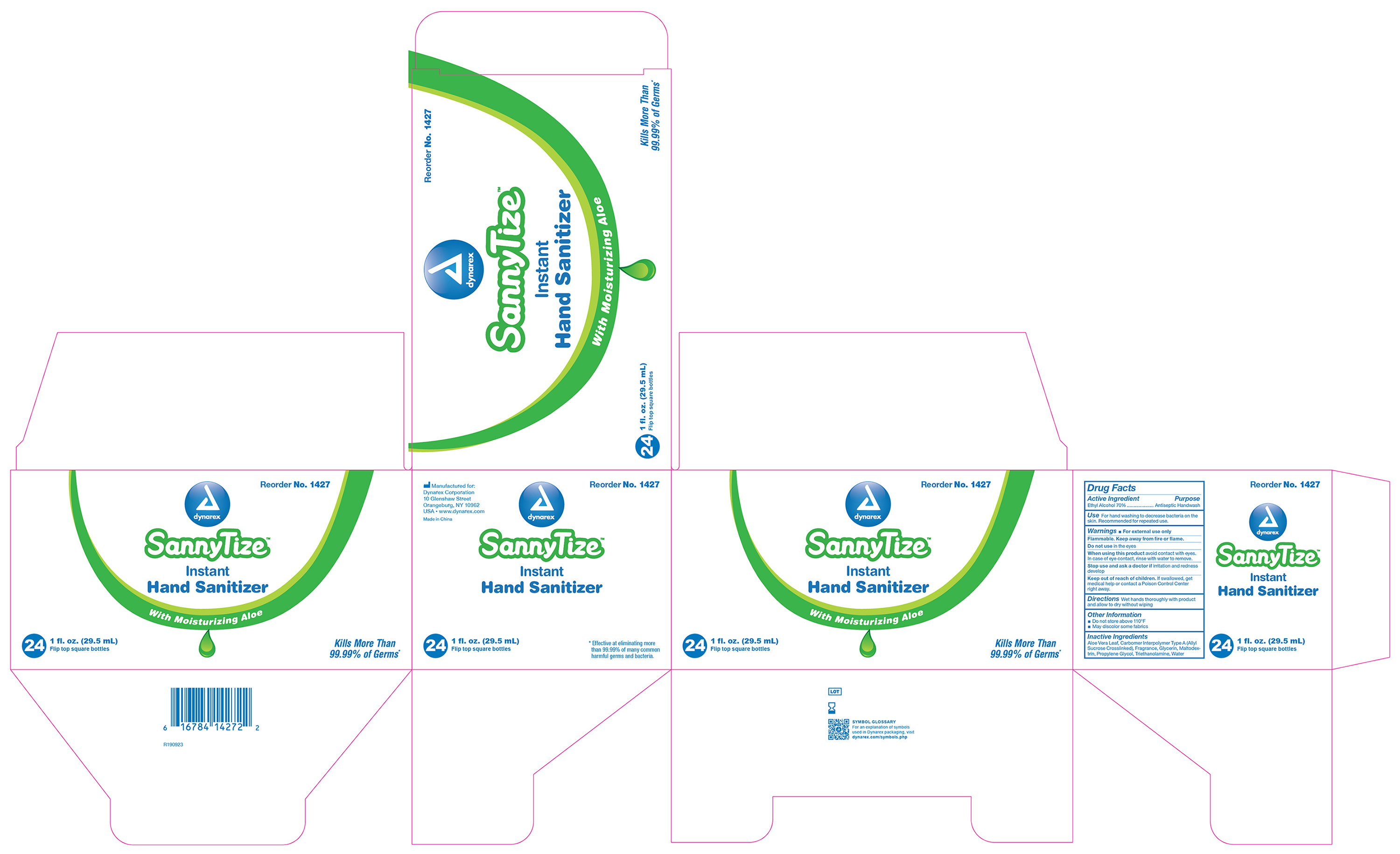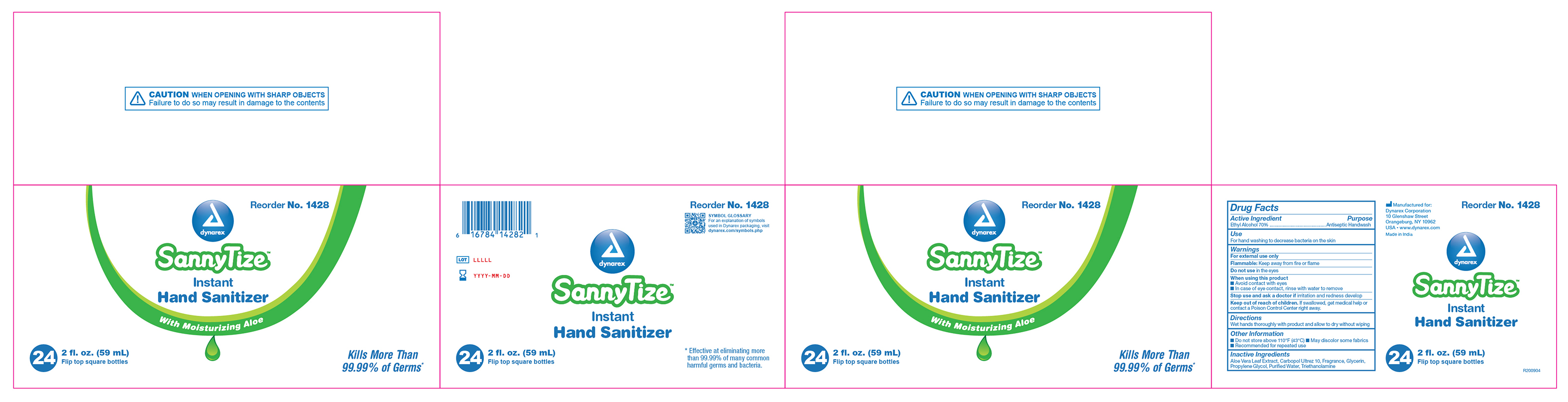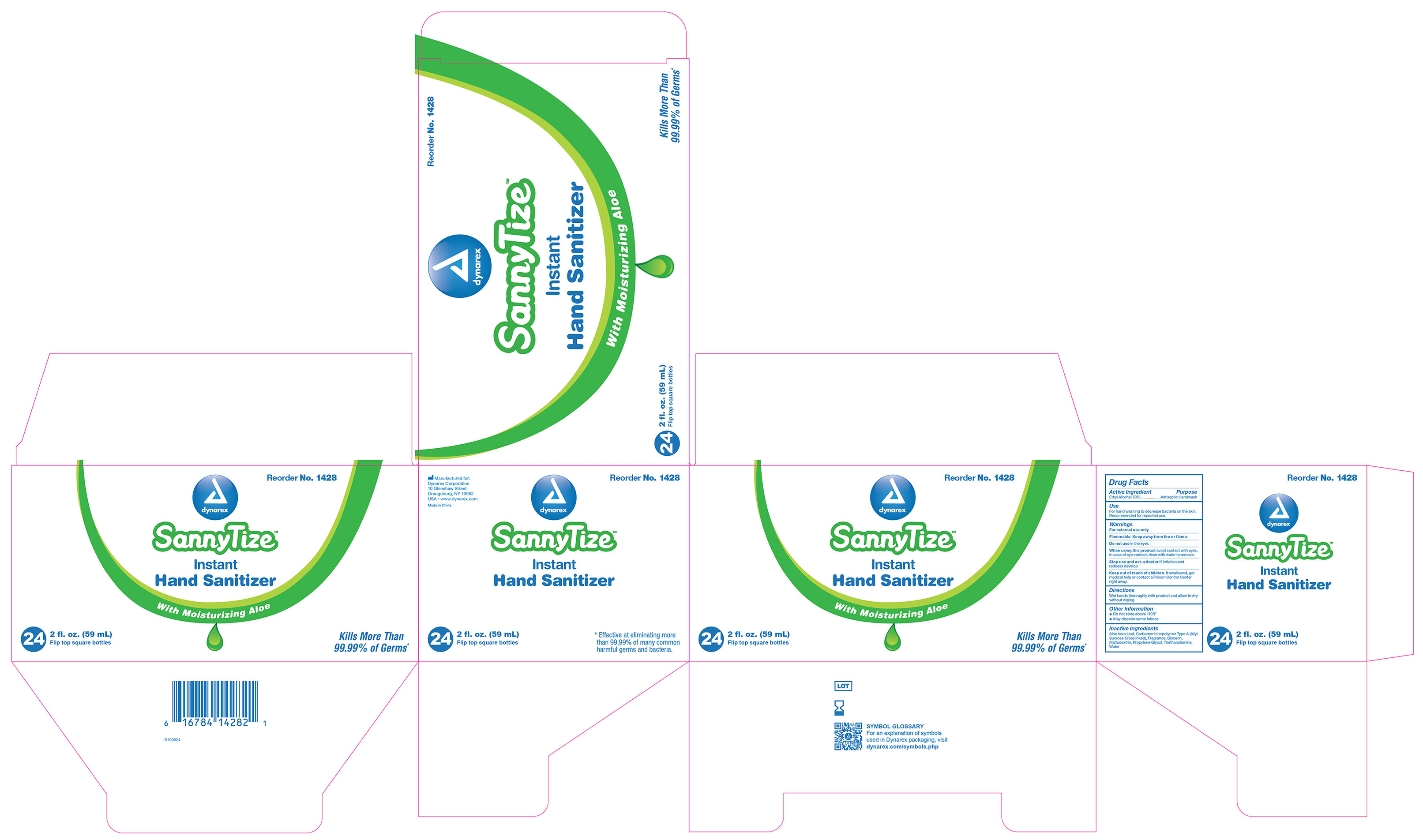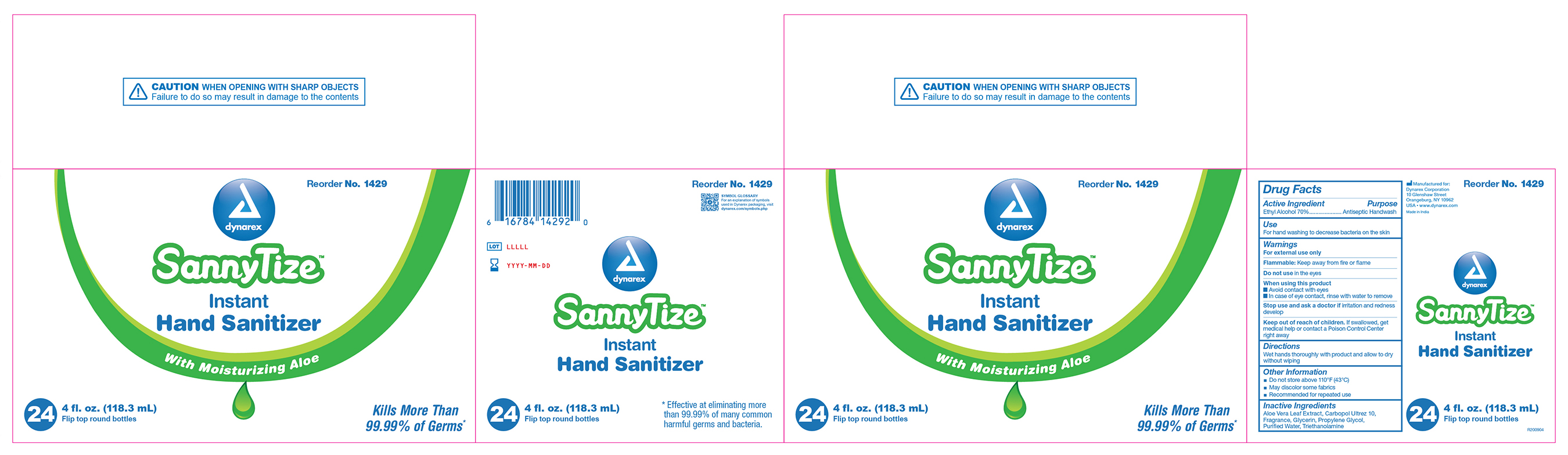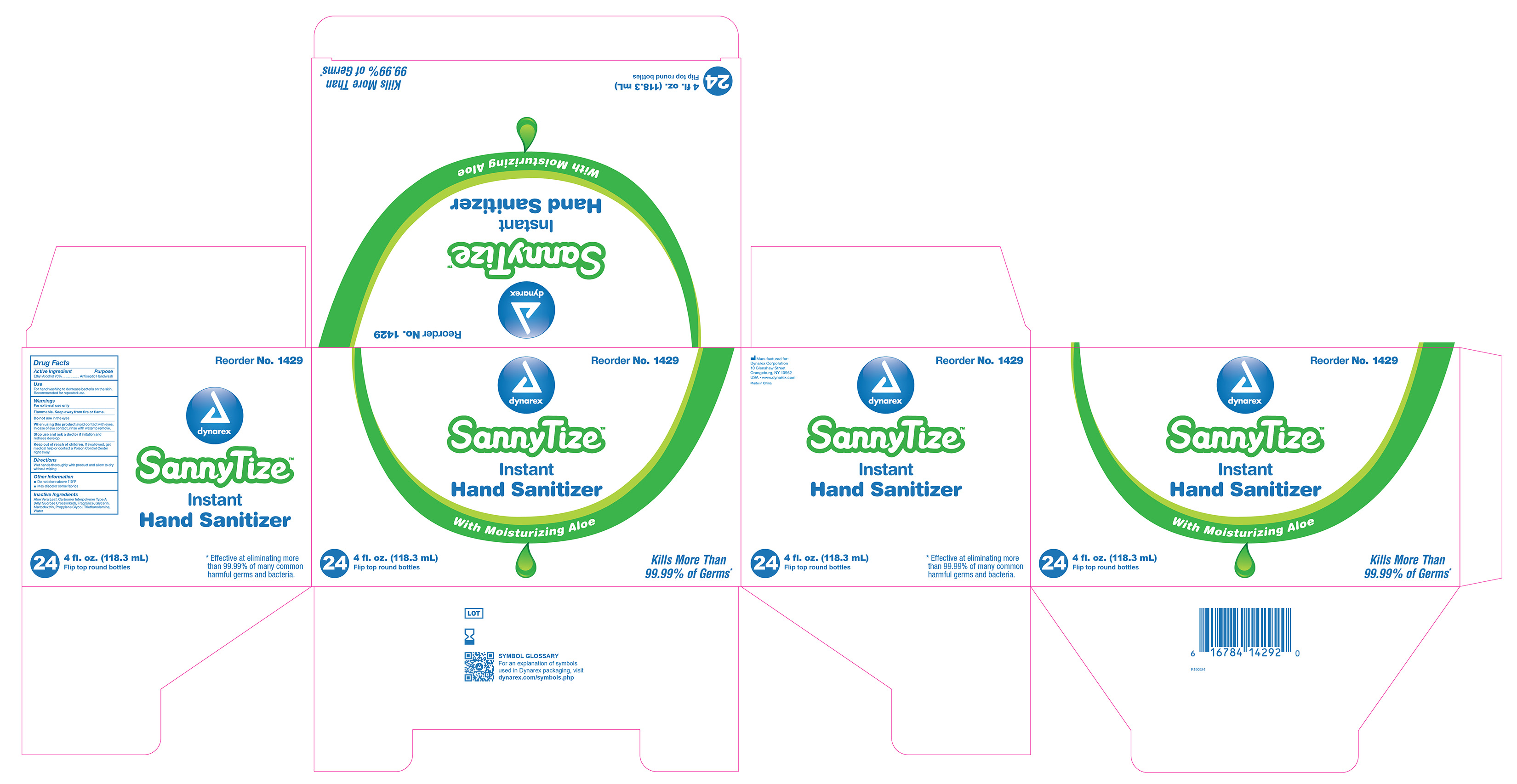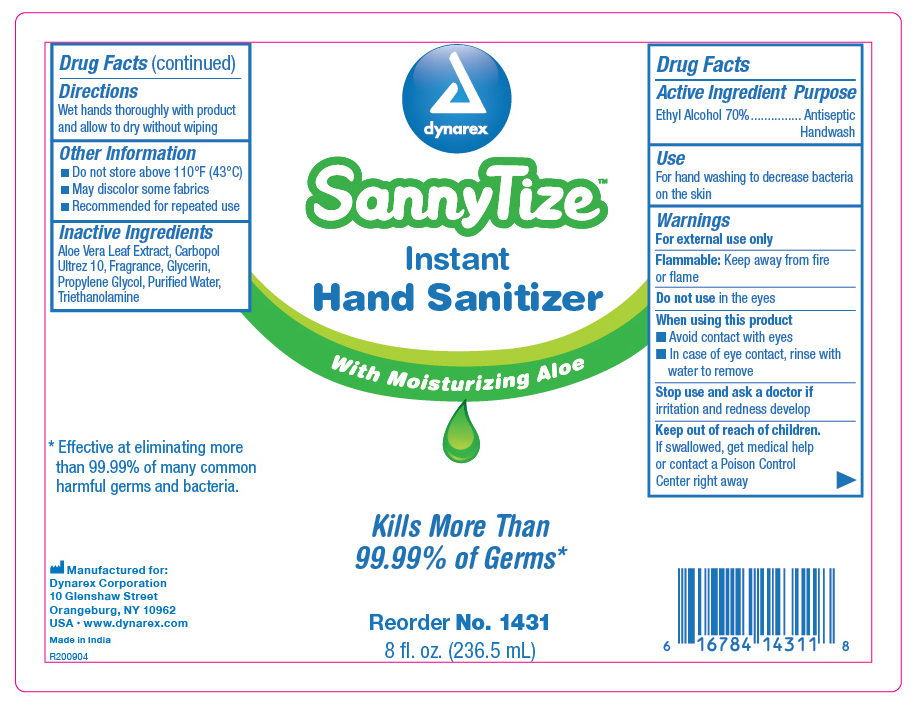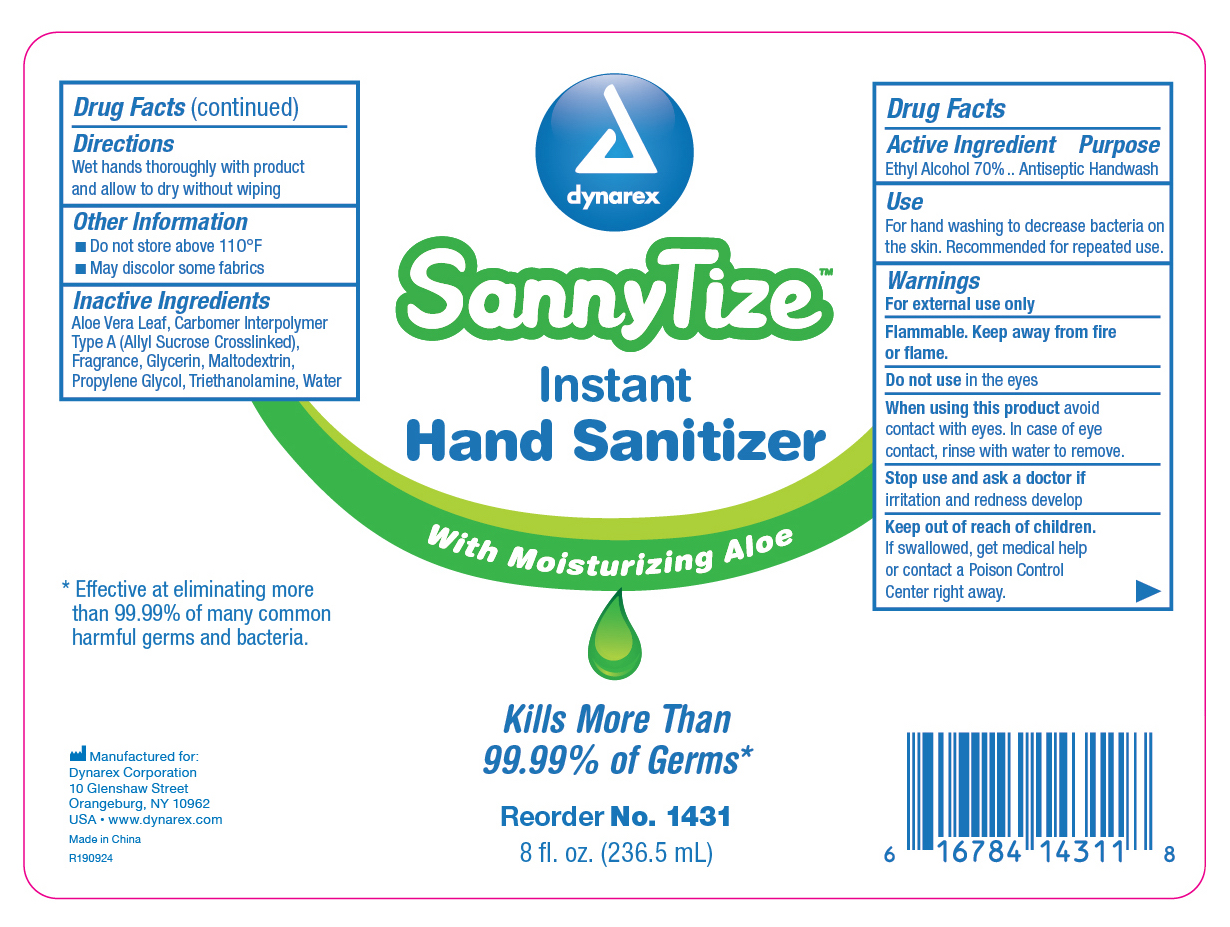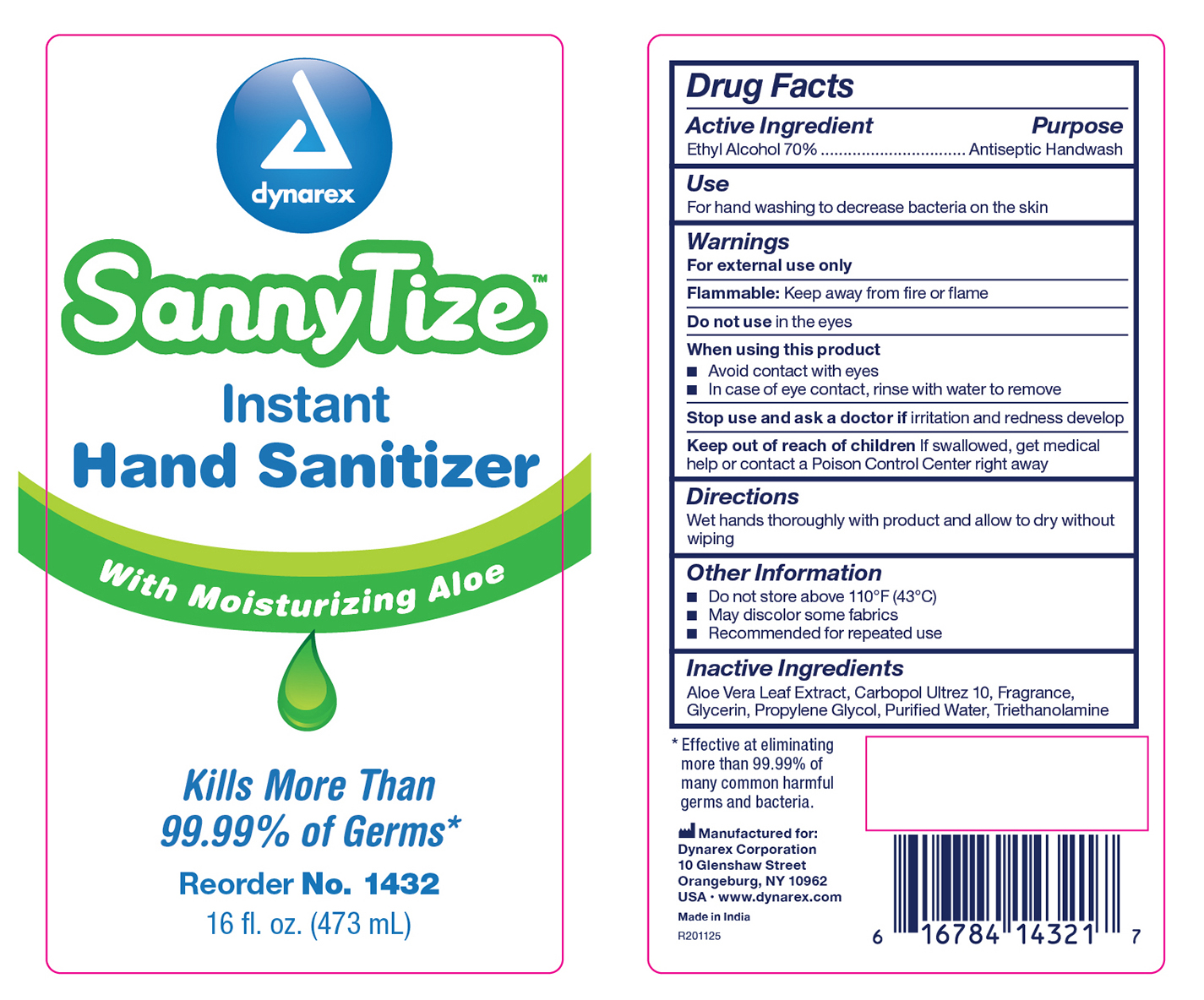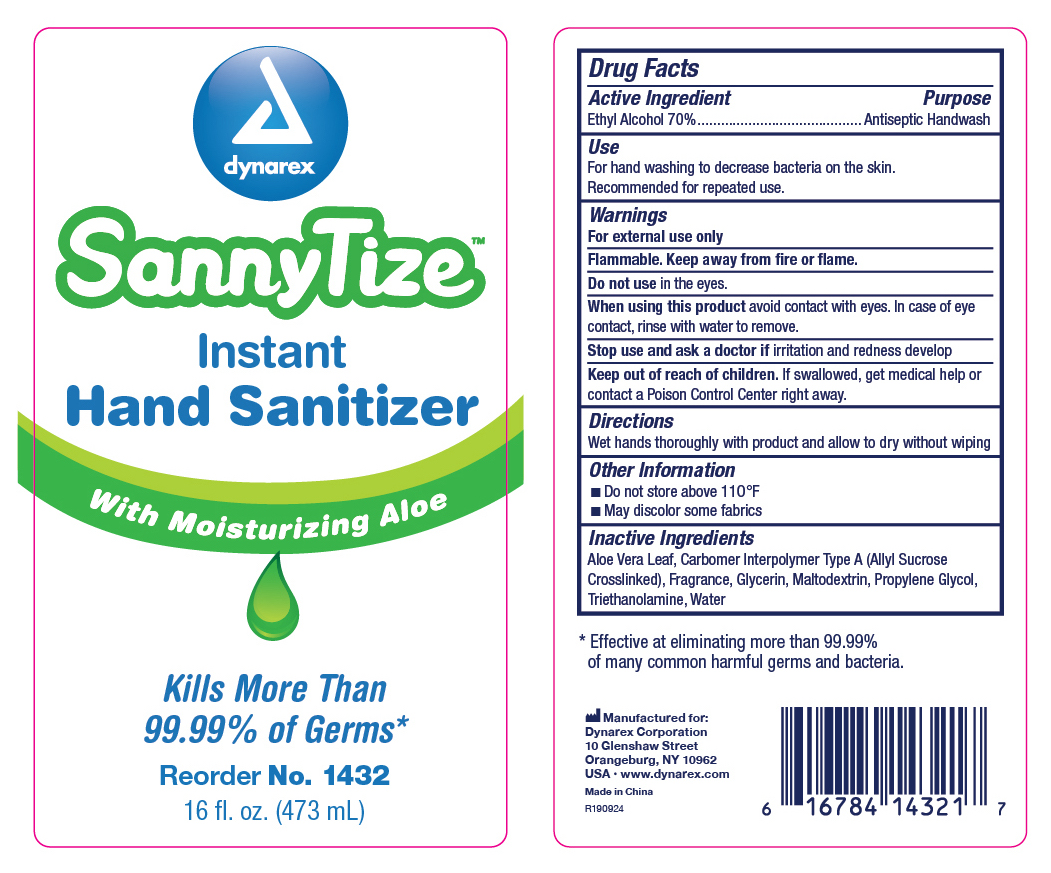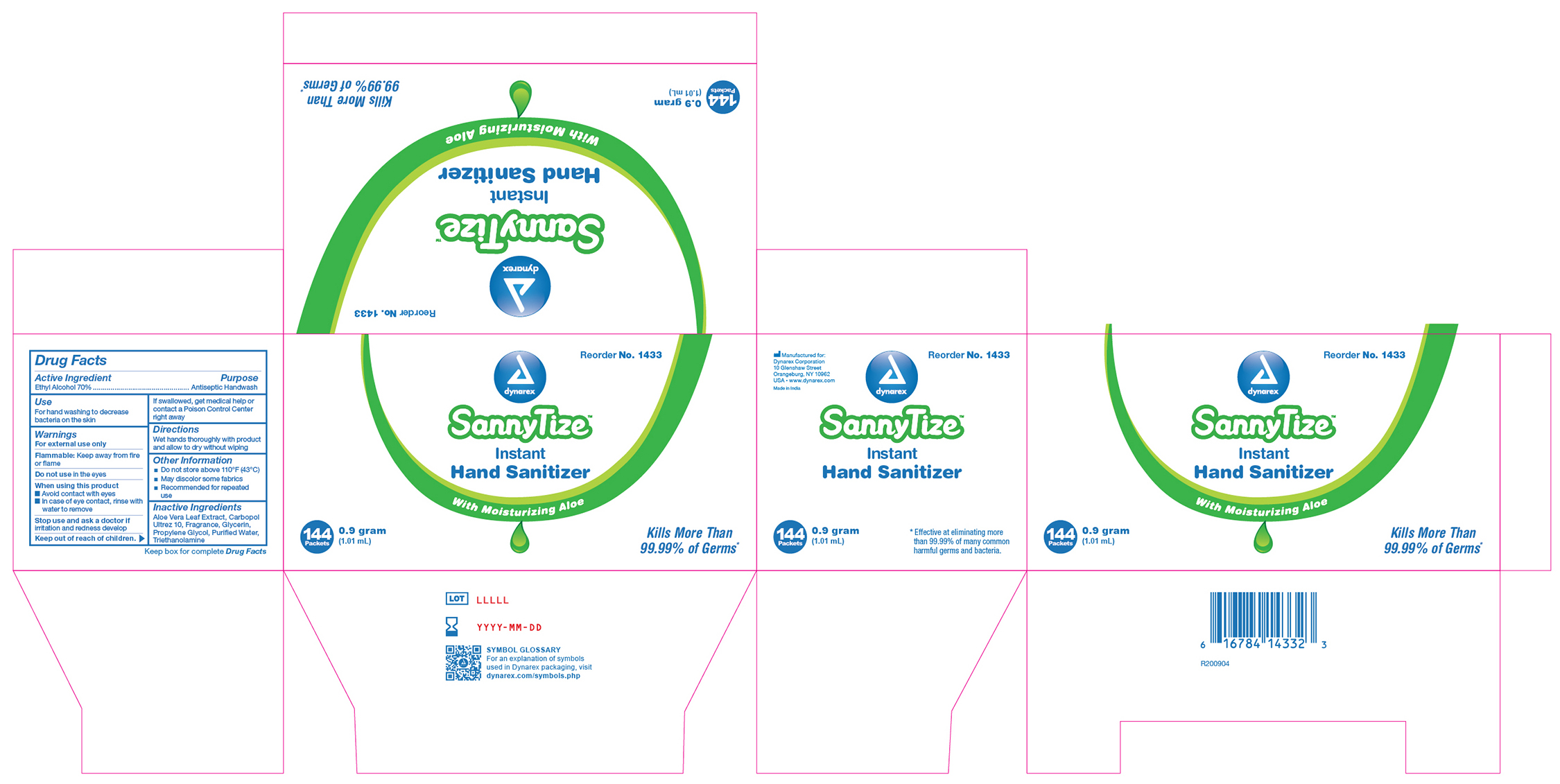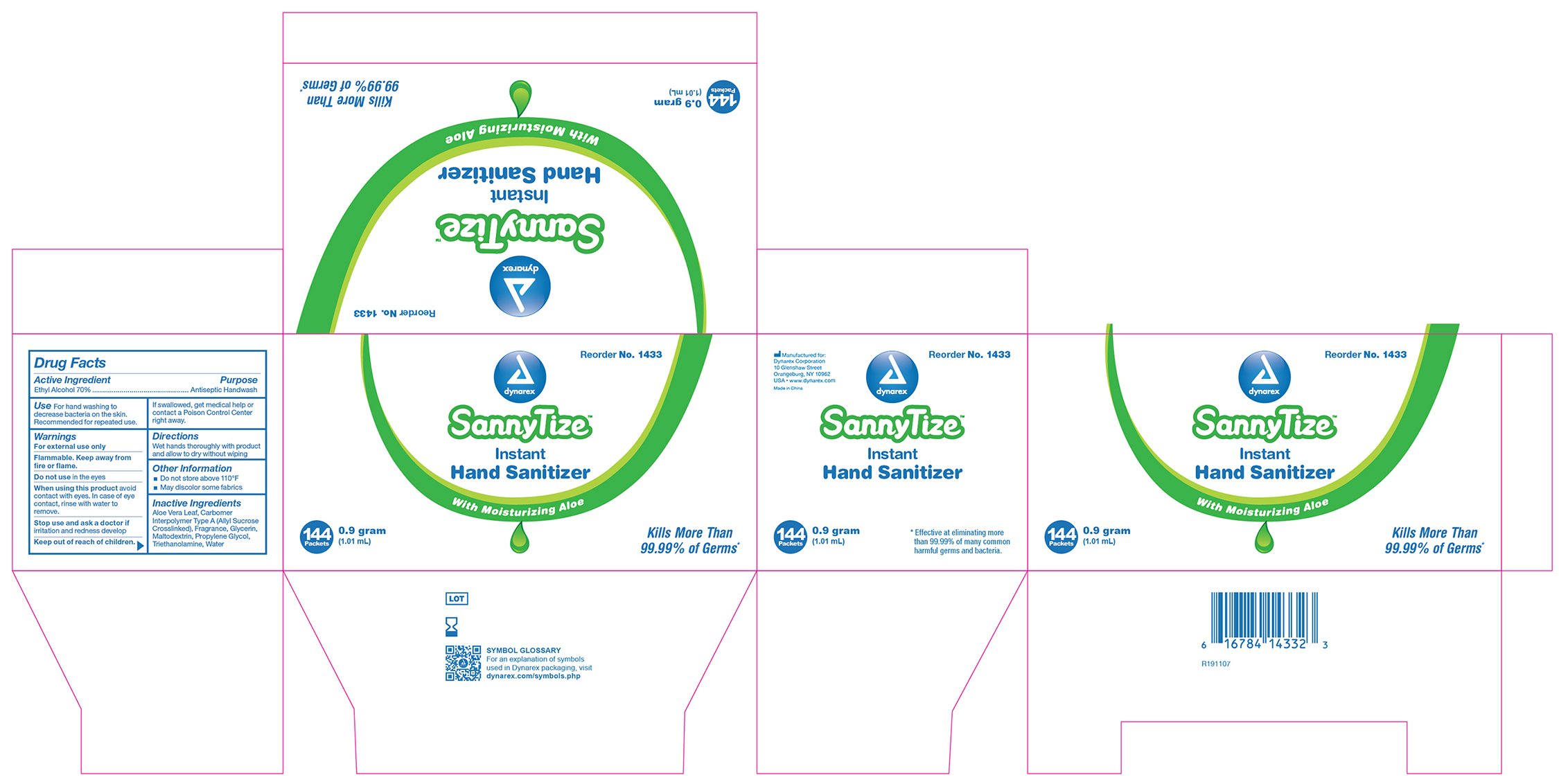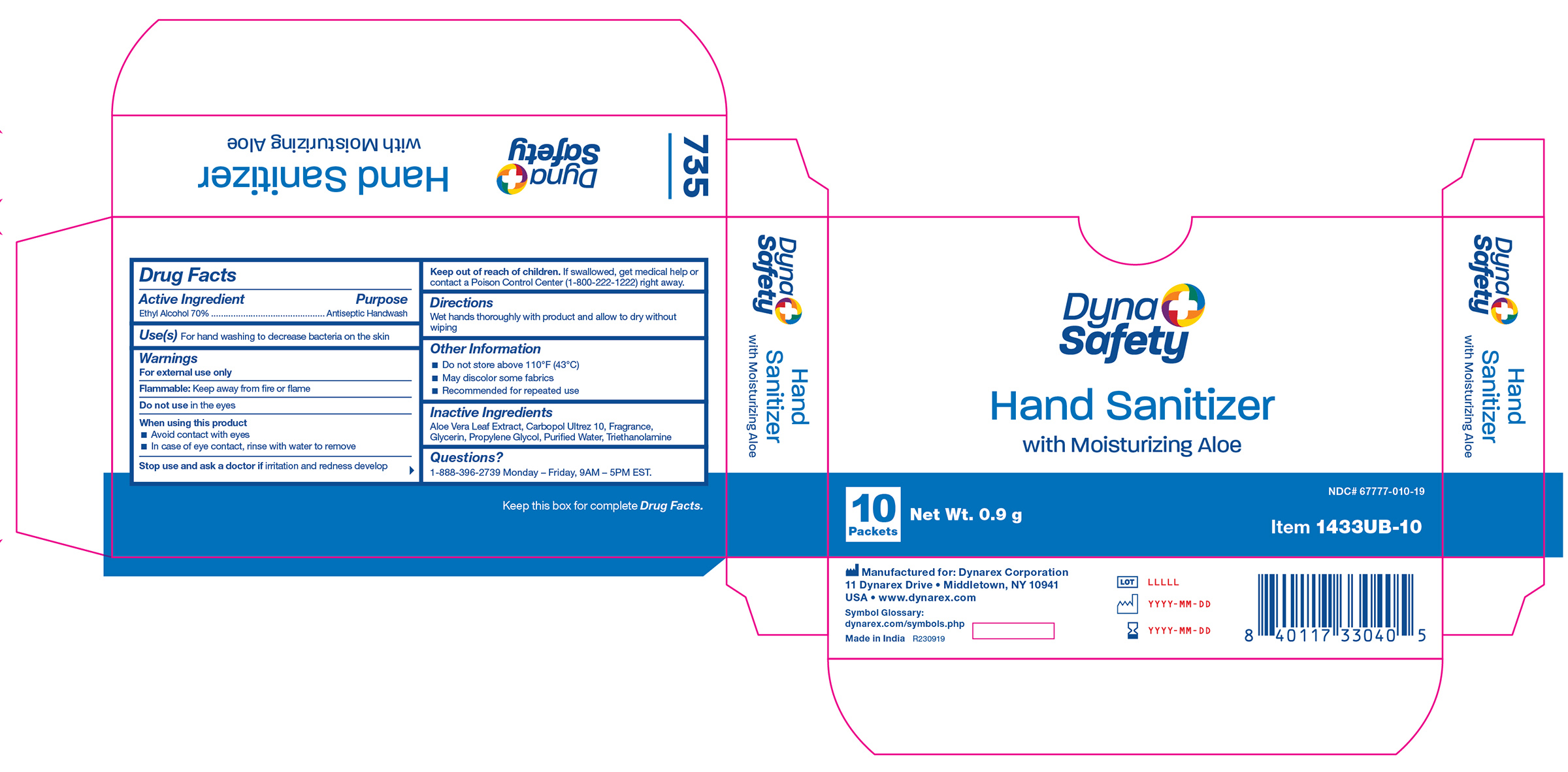 DRUG LABEL: SannyTize Hand Sanitizer
NDC: 67777-010 | Form: GEL
Manufacturer: Dynarex Corporation
Category: otc | Type: HUMAN OTC DRUG LABEL
Date: 20240124

ACTIVE INGREDIENTS: ALCOHOL 70 mL/100 mL
INACTIVE INGREDIENTS: ALOE VERA LEAF; GLYCERIN; TROLAMINE; WATER; PROPYLENE GLYCOL; CARBOMER INTERPOLYMER TYPE A (ALLYL SUCROSE CROSSLINKED)

1427 Hand Sanitizer, 1 oz. 67777-010-01, 1428 Hand Sanitizer, 2 oz. 67777-010-02
1429 Hand Sanitizer, 4 oz. 67777-010-03, 1431 Hand Sanitizer, 8 oz. 67777-010-04
1432 Hand Sanitizer, 16 oz. 67777-010-05, 1433 Hand Sanitizer, .9g 67777-010-06
1433UB-10 Hand Sanitizer, 0.9g 67777-010-20

Active Ingredient

Ethyl Alcohol 70%

Purpose

Antiseptic Handwash

Use

- For hand washing to decrease bacteria on the skin.

Warnings

For External Use Only

Flammable. Keep away from fire or flame

Do not use

In the eyes.

When using this product

• Avoid contact with eyes.

• In case of eye contact, rinse with water to remove

Stop use and ask a doctor if

Irritation and redness develop.

Keep out of reach of children.

If swallowed, get medical help or contact a Poison Control Center (1-800-222-1222) right away.

Directions

- Wet hands thoroughly with product and allow to dry without wiping

Other Information

- Do not store above 110°F (43ºC)
- May discolor some fabrics
- Recommended for repeated use

Inactive Ingredients

Aloe Vera Leaf Extract, Carbopol Ultrez 10, Fragrance, Glycerin, Propylene Glycol, Purified Water,Triethanolamine

Questions?

1-888-396-2739 Monday - Friday, 9AM - 5PM EST

Label

1428 Hand Sanitizer

Label

1427 Hand Sanitizer

Label

1429 Hand Sanitizer

Label

1431 Hand Sanitizer

Label

1432 Hand Sanitizer

Label

1433 Hand Sanitizer

Label

1431 Hand Sabitizer

Labels

1432 Hand Sanitizer

Label 1433UB-10

1433UB-10